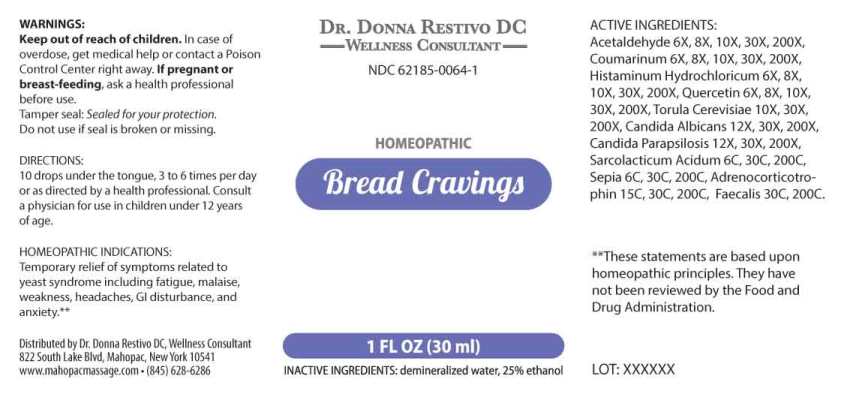 DRUG LABEL: Bread Cravings
NDC: 62185-0064 | Form: LIQUID
Manufacturer: Dr. Donna Restivo DC
Category: homeopathic | Type: HUMAN OTC DRUG LABEL
Date: 20230110

ACTIVE INGREDIENTS: ACETALDEHYDE 6 [hp_X]/1 mL; COUMARIN 6 [hp_X]/1 mL; HISTAMINE DIHYDROCHLORIDE 6 [hp_X]/1 mL; QUERCETIN 6 [hp_X]/1 mL; SACCHAROMYCES CEREVISIAE 10 [hp_X]/1 mL; CANDIDA ALBICANS 12 [hp_X]/1 mL; CANDIDA PARAPSILOSIS 12 [hp_X]/1 mL; LACTIC ACID, L- 6 [hp_C]/1 mL; SEPIA OFFICINALIS JUICE 6 [hp_C]/1 mL; CORTICOTROPIN HUMAN 15 [hp_C]/1 mL; ALCALIGENES FAECALIS 30 [hp_C]/1 mL
INACTIVE INGREDIENTS: WATER; ALCOHOL

Drug Facts:

ACTIVE INGREDIENTS:

Acetaldehyde 6X, 8X, 10X, 30X, 200X, Coumarinum 6X, 8X, 10X, 30X, 200X, Histaminum Hydrochloricum 6X, 8X, 10X, 30X, 200X, Quercetin 6X, 8X, 10X, 30X, 200X, Torula Cerevisiae 10X, 30X, 200X, Candida Albicans 12X, 30X, 200X, Candida Parapsilosis 12X, 30X, 200X, Adrenocorticotrophin 6C, 30C, 200C, Sarcolacticum Acidum 6C, 30C, 200C, Sepia 6C, 30C, 200C, Adrenocorticotrophin 15C, 30C, 200C, Faecalis (Alkaligenes) 30C, 200C.

HOMEOPATHIC INDICATIONS:

Temporary relief of symptoms related to yeast syndrome including fatigue, malaise, weakness, headaches, GI disturbance, and anxiety.**

**These statements are based upon homeopathic principles. They have not been reviewed by the Food and Drug Administration.

WARNINGS:

Keep out of reach of children. In case of overdose, get medical help or contact a Poison Control Center right away.

If pregnant or breast-feeding, ask a health professional before use.

Tamper seal: Sealed for your protection.

Do not use if seal is broken or missing.

Keep out of reach of children. In case of overdose, get medical help or contact a Poison Control Center right away.

DIRECTIONS:

10 drops under the tongue, 3 to 6 times per day or as directed by a health professional. Consult a physician for use in children under 12 years of age.

HOMEOPATHIC INDICATIONS:

Temporary relief of symptoms related to yeast syndrome including fatigue, malaise, weakness, headaches, GI disturbance, and anxiety.**

**These statements are based upon homeopathic principles. They have not been reviewed by the Food and Drug Administration.

INACTIVE INGREDIENTS:

demineralized water, 25% ethanol

QUESTIONS:

Distributed by Dr. Donna Restivo DC, Wellness Consultant

822 South Lake Blvd, Mahopac, New York 10541

www.mahopacmassage.com (845) 628-6286

PACKAGE LABEL DISPLAY:

DR. DONNA RESTIVO DC

WELLNESS CONSULTANT

NDC 62185-0064-1

HOMEOPATHIC

Bread Cravings

1 FL OZ (30 ml)